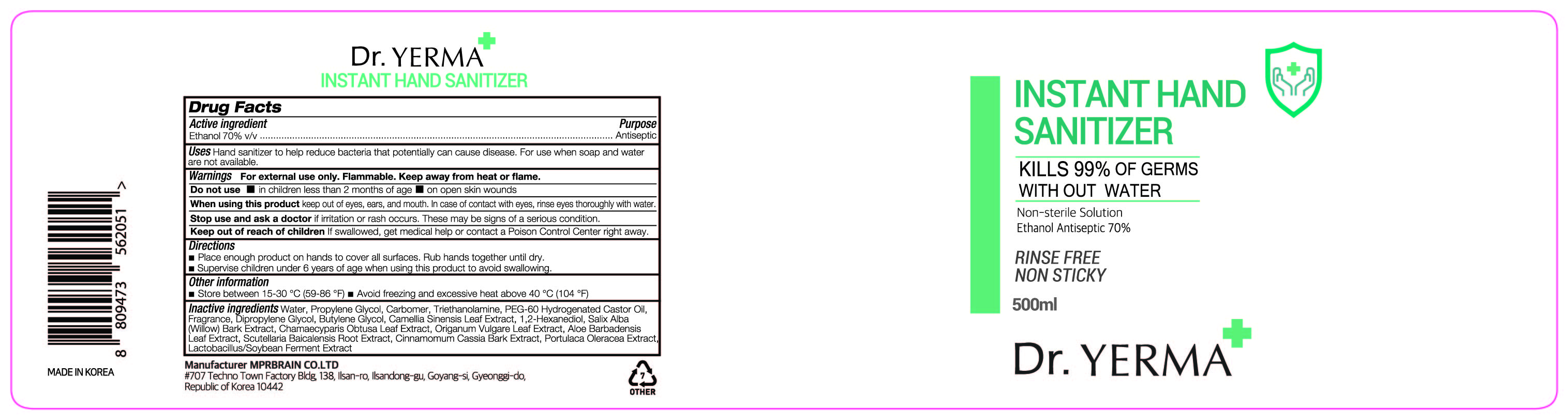 DRUG LABEL: Dr. YERMA INSTANT HAND SANITIZER
NDC: 74741-7502 | Form: GEL
Manufacturer: MPRBRAIN CO.LTD
Category: otc | Type: HUMAN OTC DRUG LABEL
Date: 20200612

ACTIVE INGREDIENTS: ALCOHOL 350 mL/500 mL
INACTIVE INGREDIENTS: SOYBEAN GERM; DIPROPYLENE GLYCOL; CARBOMER HOMOPOLYMER, UNSPECIFIED TYPE; GREEN TEA LEAF; PEG-60 HYDROGENATED CASTOR OIL; BUTYLENE GLYCOL; WATER; PROPYLENE GLYCOL; SCUTELLARIA BAICALENSIS ROOT; CHINESE CINNAMON; PURSLANE; TROLAMINE; ALOE VERA LEAF; OREGANO; SALIX ALBA BARK; CHAMAECYPARIS OBTUSA LEAF; 1,2-HEXANEDIOL

Dr. YERMA INSTANT HAND SANITIZER 500 ml : 74741-7502-1 (Bottle)